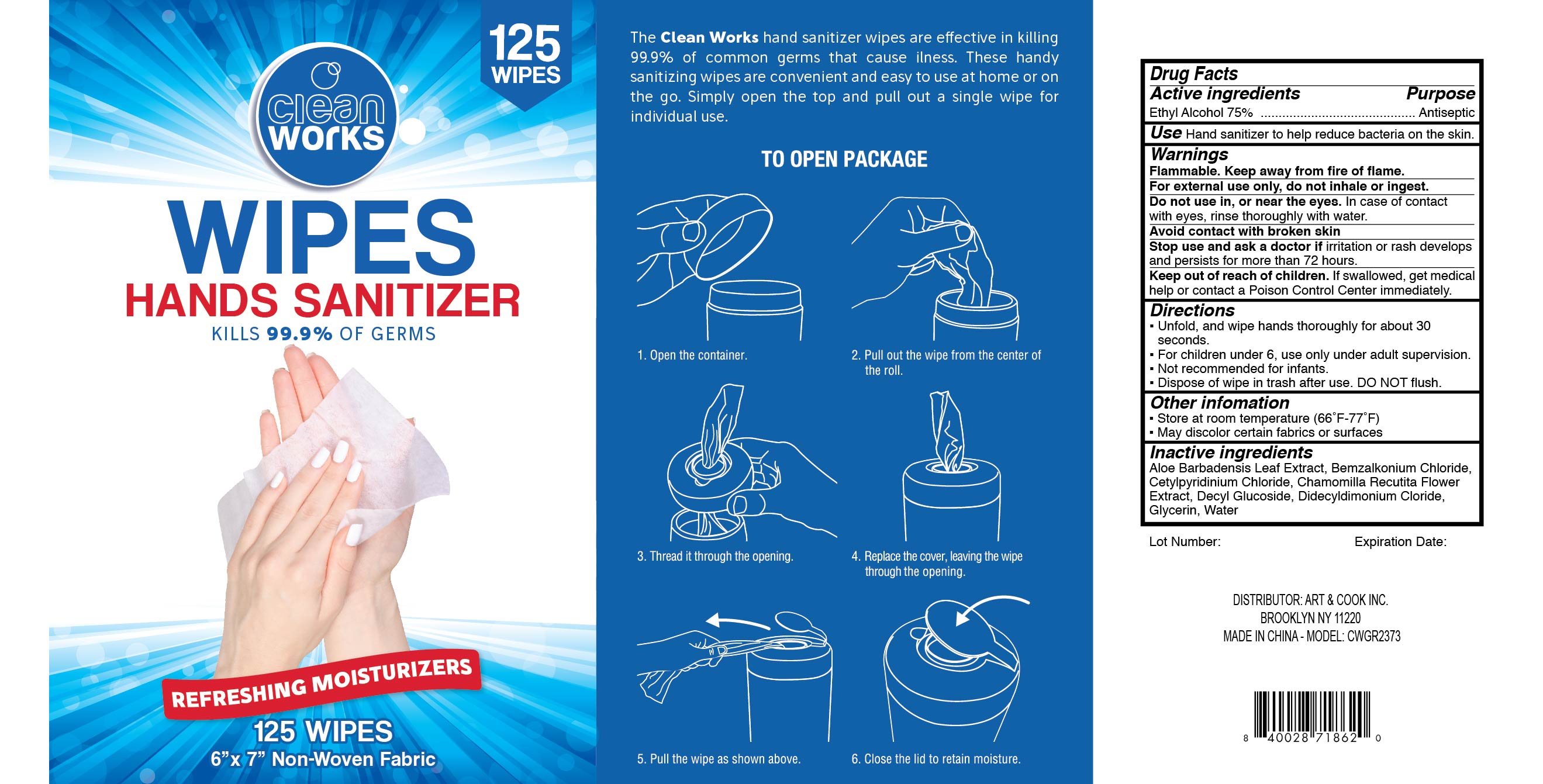 DRUG LABEL: cleanworks Hand Sanitizer Wipes
NDC: 78332-002 | Form: CLOTH
Manufacturer: Art and Cook Inc.
Category: otc | Type: HUMAN OTC DRUG LABEL
Date: 20200617

ACTIVE INGREDIENTS: ALCOHOL 0.75 mL/1 1
INACTIVE INGREDIENTS: WATER; ALOE VERA LEAF; CHAMOMILE; DECYL GLUCOSIDE; BENZALKONIUM CHLORIDE; CETYLPYRIDINIUM CHLORIDE ANHYDROUS; DIDECYLDIMONIUM CHLORIDE; GLYCERIN

cleanworks hands wipes

Active Ingredient

Ethyl Alcohol 75%

Purpose

Antiseptic

Use

Hand sanitizer to help reduce bacteria on the skin.

Warnings

Flammable. Keep away from fire or flame. For external use only, do not inhale or ingest

Do not use

in or near eyes. In case of contact with eyes, rinse thoroughly with water. Avoid contact with broken skin

Stop use and ask a doctor if

irritation or rash develops and persists for more than 72 hours

Keep out of reach of children

If swallowed, get medical help or contact the Poison Control Center immediately.

Directions

- Unfold, and wipe hands thoroughly for about 30 seconds
- For children under 6, use only under adult supervision
- Not recommended for infants
- Dispose of wipe in trash after use. DO NOT flush

Other information

- Store at room temperature (66ºF-77ºF)
- May discolor certain fabrics or surfaces

Inactive ingredients

Aloe Barbadensis Leaf Extract, Benzalkonium Chloride, Cetylpyridinium Chloride, Chamomilla Recutita Flower Extract, Decyl Glucoside, Didecyldimonium Chloride, Glycerin, Water